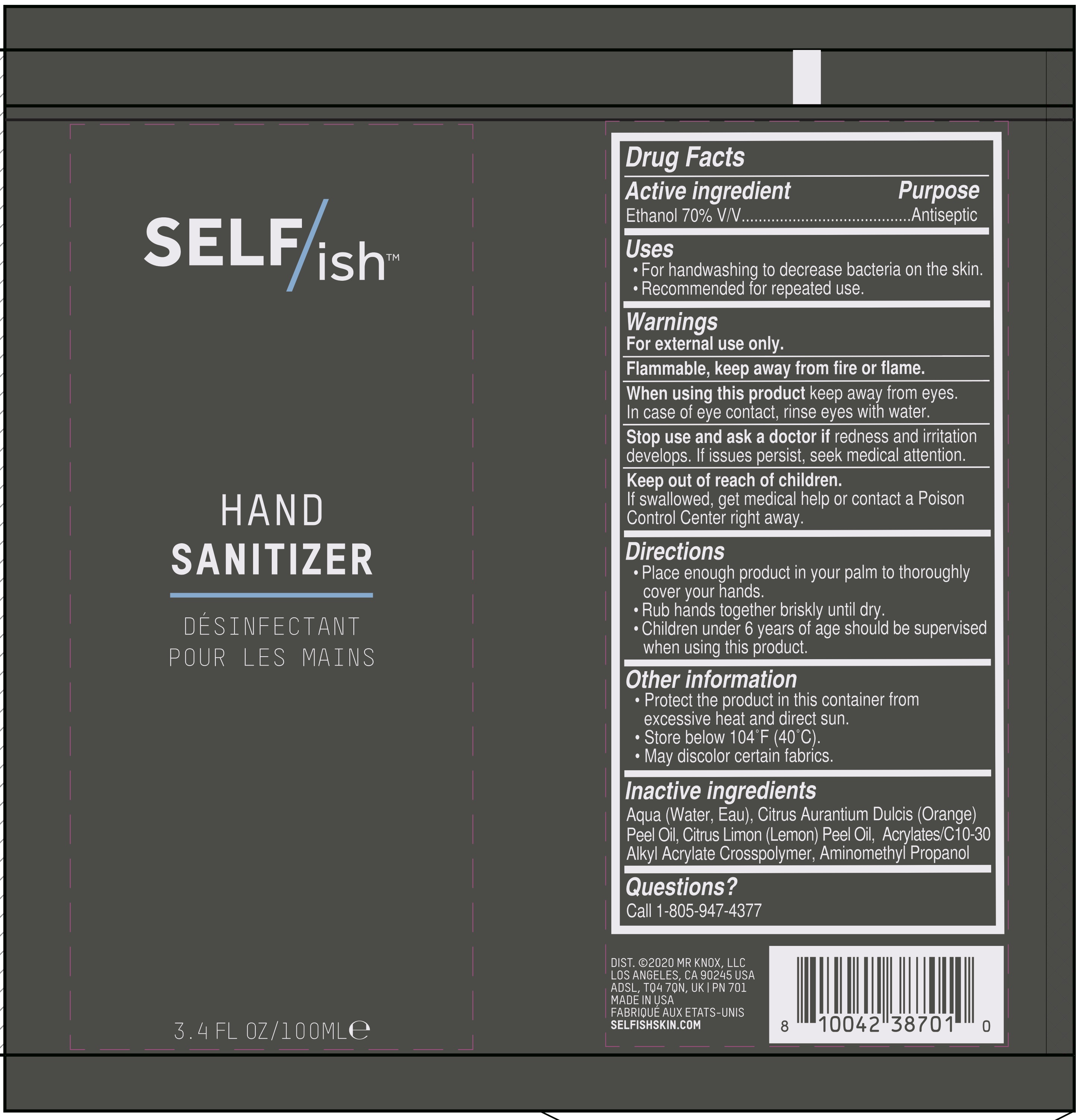 DRUG LABEL: Hand Sanitizer
NDC: 78831-701 | Form: GEL
Manufacturer: Mr Knox LLP.
Category: otc | Type: HUMAN OTC DRUG LABEL
Date: 20200608

ACTIVE INGREDIENTS: ALCOHOL 70 mL/100 mL
INACTIVE INGREDIENTS: WATER

Hand Sanitizer Gel

Active Ingredient(s)

Alcohol 70% v/v. Purpose: Antimicrobial

Purpose

Antimicrobial, Hand Sanitizer

Use

For handwashing to decrease bacteria on the skin.

Recommended for repeated use.

Warnings

For external use only. Flammable. Keep away from fire or flame

When using this product keep away from eyes. In case of eye contact, rinse eyes with water.

Stop use and ask a doctor if redness and irritation develops. If issues persist, seek medical attention.

Keep out of reach of children. If swallowed, get medical help or contact a Poison Control Center right away.

Stop use and ask a doctor if redness and irritation develops. If issues persist, seek medical attention.

Keep out of reach of children. If swallowed, get medical help or contact a Poison Control Center right away.

Directions

- Place enough product in your palm to thoroughly cover your hands.
- Rub hands together briskly until dry.
- Children under 6 years of age should be supervised when using this product.

Other information

- Protect the product in this container from excessive hear and direct sun.
- Store below 104F (40C).
- May discolor certain fabrics.

Inactive ingredients

Aqua (Water, Eau), Citrus Aurantium Dulcis (Orange) Peel Oil, Citrus Limon (Lemon) Peel Oil, Acrylates/C10-30 Alkyl Acrylate Crosspolymer, Aminomethyl Propanol

Package Label - Principal Display Panel

100 mL NDC: 78831-701-01